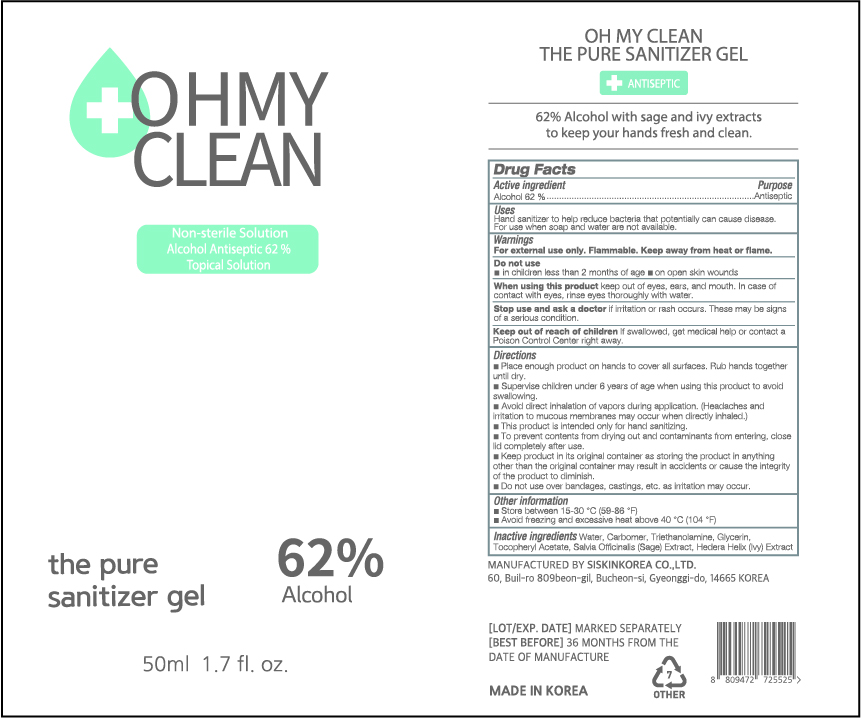 DRUG LABEL: OH MY CLEAN THE PURE SANITIZER Gel
NDC: 74514-5062 | Form: GEL
Manufacturer: SISKINKOREA CO.,LTD.
Category: otc | Type: HUMAN OTC DRUG LABEL
Date: 20200514

ACTIVE INGREDIENTS: ALCOHOL 31 mL/50 mL
INACTIVE INGREDIENTS: TROLAMINE; GLYCERIN; .ALPHA.-TOCOPHEROL ACETATE; SAGE; WATER; HEDERA HELIX LEAF; CARBOMER HOMOPOLYMER, UNSPECIFIED TYPE

Packaging change 50ml_62%_gel_OH MY CLEAN THE PURE SANITIZER GEL [74514-0056-1] -> 74514-5062-1